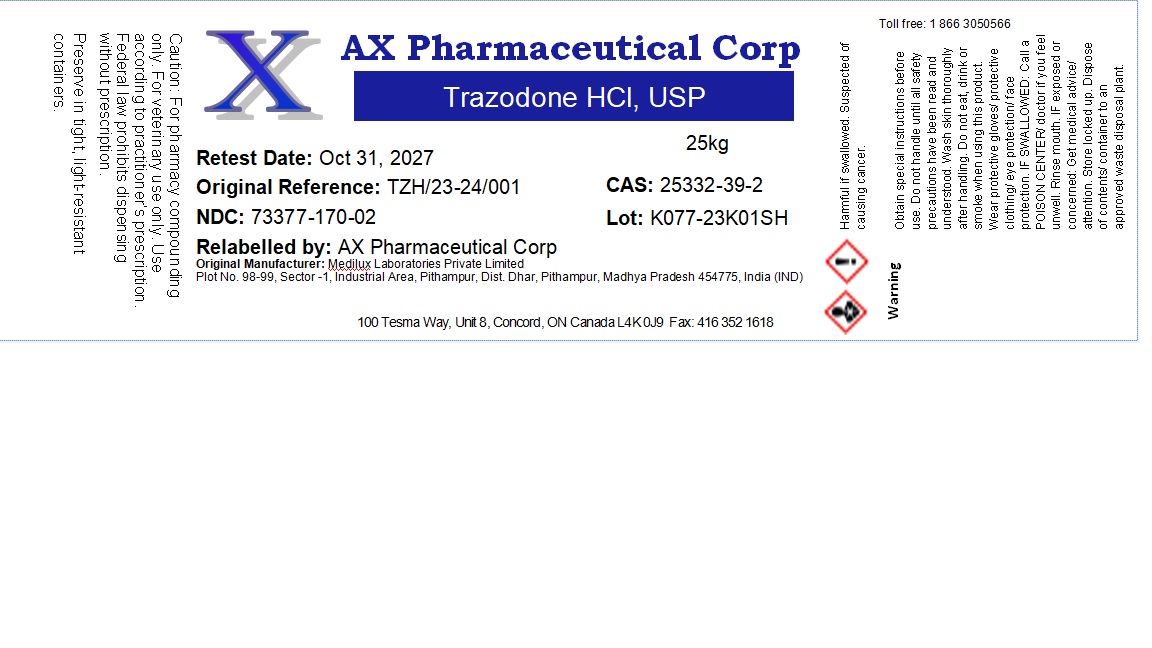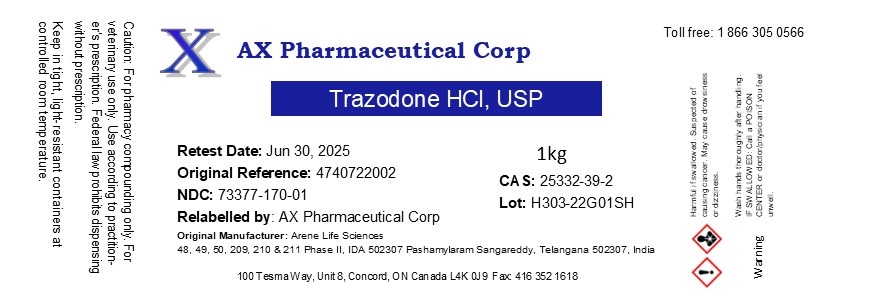 DRUG LABEL: Trazodone HCl
NDC: 73377-170 | Form: POWDER
Manufacturer: AX Pharmaceutical Corp
Category: other | Type: BULK INGREDIENT - ANIMAL DRUG
Date: 20250423

ACTIVE INGREDIENTS: TRAZODONE HYDROCHLORIDE 1 g/1 g

Trazodone HCl